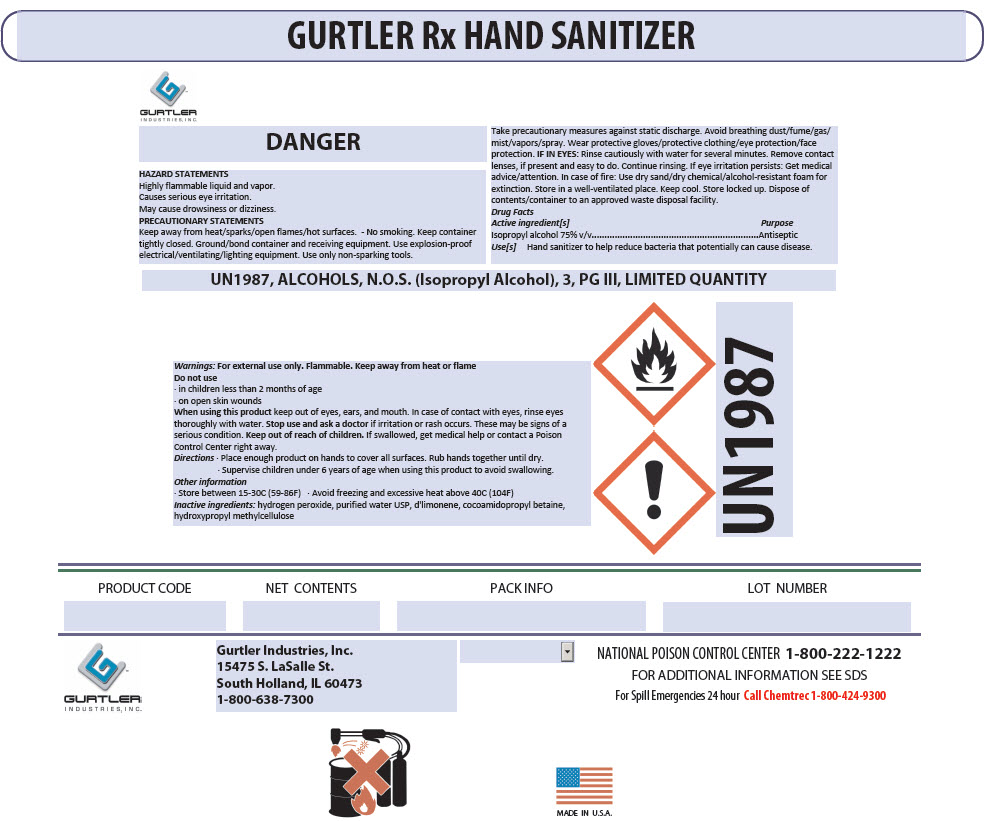 DRUG LABEL: Gurtler Rx Hand Sanitizer
NDC: 54555-132 | Form: LIQUID
Manufacturer: Brainerd Chemical Company Inc.,
Category: otc | Type: HUMAN OTC DRUG LABEL
Date: 20200701

ACTIVE INGREDIENTS: alcohol 750 mL/1 L
INACTIVE INGREDIENTS: Cocamidopropyl Betaine; hydrogen peroxide; water; LIMONENE OXIDE, TRANS-(+)-; HYDROXYMETHYL CELLULOSE

Gurtler Rx Hand Sanitizer

Drug Facts

Active ingredient[s]

Isopropyl alcohol 75% v/v

Purpose

Antiseptic

Use[s]

Hand sanitizer to help reduce bacteria that potentially can cause disease.

Warnings

For external use only. Flammable. Keep away from heat or flame

Do not use

- in children less than 2 months of age
- on open skin wounds

When using this product keep out of eyes, ears, and mouth. In case of contact with eyes, rinse eyes thoroughly with water.

Stop use and ask a doctor if irritation or rash occurs. These may be signs of a serious condition.

Keep out of reach of children. If swallowed, get medical help or contact a Poison Control Center right away.

Directions

- Place enough product on hands to cover all surfaces. Rub hands together until dry.
- Supervise children under 6 years of age when using this product to avoid swallowing.

Other information

- Store between 15-30C (59-86F)
- Avoid freezing and excessive heat above 40C (104F)

Inactive ingredients

hydrogen peroxide, purified water USP, d'limonene, cocoamidopropyl betaine, hydroxypropyl methylcellulose

PRINCIPAL DISPLAY PANEL - 3.785 L Jug Label

GURTLER
INDUSTRIES, INC.

GURTLER Rx HAND SANITIZER

DANGER

HAZARD STATEMENTS
Highly flammable liquid and vapor.
Causes serious eye irritation.
May cause drowsiness or dizziness.

PRECAUTIONARY STATEMENTS
Keep away from heat/sparks/open flames/hot surfaces. - No smoking. Keep container
tightly closed. Ground/bond container and receiving equipment. Use explosion-proof
electrical/ventilating/lighting equipment. Use only non-sparking tools.

Take precautionary measures against static discharge. Avoid breathing dust/fume/gas/
mist/vapors/spray. Wear protective gloves/protective clothing/eye protection/face
protection. IF IN EYES: Rinse cautiously with water for several minutes. Remove contact
lenses, if present and easy to do. Continue rinsing. If eye irritation persists: Get medical
advice/attention. In case of fire: Use dry sand/dry chemical/alcohol-resistant foam for
extinction. Store in a well-ventilated place. Keep cool. Store locked up. Dispose of
contents/container to an approved waste disposal facility.

UN1987, ALCOHOLS, N.O.S. (Isopropyl Alcohol), 3, PG III, LIMITED QUANTITY

!
UN1987

PRODUCT CODE
NET CONTENTS
PACK INFO
LOT NUMBER

Gurtler Industries, Inc.
15475 S. LaSalle St.
South Holland, IL 60473
1-800-638-7300

NATIONAL POISON CONTROL CENTER 1-800-222-1222
FOR ADDITIONAL INFORMATION SEE SDS
For Spill Emergencies 24 hour Call Chemtrec 1-800-424-9300

MADE IN U.S.A.